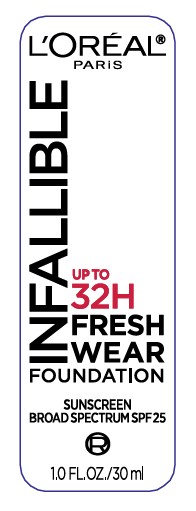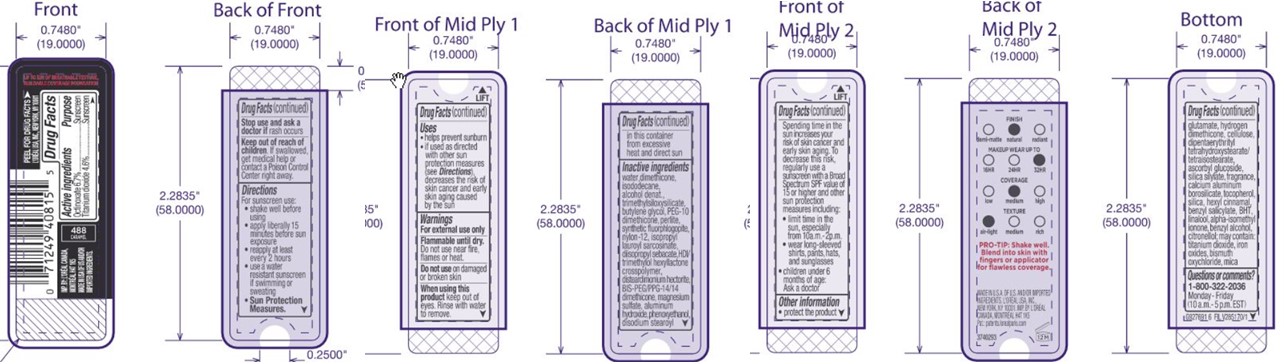 DRUG LABEL: LOreal Paris Infallible UP TO 32H Fresh Wear Foundation Broad Spectrum SPF 25 Sunscreen
NDC: 49967-815 | Form: LIQUID
Manufacturer: L'Oreal USA Products Inc
Category: otc | Type: HUMAN OTC DRUG LABEL
Date: 20240628

ACTIVE INGREDIENTS: OCTINOXATE 67 mg/1 mL; TITANIUM DIOXIDE 46 mg/1 mL
INACTIVE INGREDIENTS: WATER; DIMETHICONE; ISODODECANE; ALCOHOL; BUTYLENE GLYCOL; PERLITE; NYLON-12; ISOPROPYL LAUROYL SARCOSINATE; DIISOPROPYL SEBACATE; HEXAMETHYLENE DIISOCYANATE/TRIMETHYLOL HEXYLLACTONE CROSSPOLYMER; DISTEARDIMONIUM HECTORITE; BIS-PEG/PPG-14/14 DIMETHICONE; MAGNESIUM SULFATE, UNSPECIFIED FORM; ALUMINUM HYDROXIDE; PHENOXYETHANOL; DISODIUM STEAROYL GLUTAMATE; POWDERED CELLULOSE; DIPENTAERYTHRITYL TETRAHYDROXYSTEARATE/TETRAISOSTEARATE; ASCORBYL GLUCOSIDE; CALCIUM ALUMINUM BOROSILICATE; TOCOPHEROL; SILICON DIOXIDE; .ALPHA.-HEXYLCINNAMALDEHYDE; BENZYL SALICYLATE; BUTYLATED HYDROXYTOLUENE; LINALOOL, (+/-)-; ISOMETHYL-.ALPHA.-IONONE; BENZYL ALCOHOL; .BETA.-CITRONELLOL, (R)-; FERRIC OXIDE RED; BISMUTH OXYCHLORIDE; MICA

Drug Facts

Active ingredients

Octinoxate 6.7%

Titanium dioxide 4.6%

Purpose

Sunscreen

Uses

- helps prevent sunburn
- if used as directed with other sun protection measures (see Directions), decreases the risk of skin cancer and early skin aging caused by the sun

Warnings

For external use only

Flammable until dry.

Do not use near fire, flames or heat.

Do not use

on damaged or broken skin

When using this product

keep out of eyes. Rinse with water to remove.

Stop use and ask a doctor if

rash occurs

Keep out of reach of children.

If swallowed, get medical help or contact a Poison Control Center right away.

Directions

For sunscreen use:

- shake well beore using
- apply liberally 15 minutes before sun exposure
- reapply at least every 2 hours
- use a water resistant sunscren if swimming or sweating
- Sun Protection Measures. Spending time in the sun increases your risk of skin cancer and early skin aging. To decrease this risk, regularly use a sunscreen with a Broad Spectrum SPF value of 15 or higher and other sun protection measures including:
- limit time in the sun, especially from 10 a.m. - 2 p.m.
- wear long-sleeved shirts, pants, hats, and sunglasses
- children under 6 months of age: Ask a doctor

Other information

- protect the product in this container from excessive heat and direct sun

Inactive ingredients

water, dimethicone, isododecane, alcohol denat., trimethylsiloxysilicate, butylene glycol, PEG-10 dimethicone, perlite, synthetic fluorphlogopite, nylon-12, isopropyl lauroyl sarcosinate, diisopropyl sebacate, HDI/trimethylol hexyllactone crosspolymer, disteardimonium hectorite, BIS-PEG/PPG-14/14 dimethicone, magnesium sulfate, aluminum hydroxide, phenoxyethanol, disodium stearoyl glutamate, hydrogen dimethicone, cellulose, dipentaerythrityl tetrahydroxystearate/tetraisostearate, ascorbyl glucoside, silica silylate, fragrance, calcium aluminum borosilicate, tocopherol, silica, hexyl cinnamal, benzyl salicylate, BHT, linalool, alpha-isomethyl ionone, benzyl alcohol, citronellol; may contain: titanium dioxide, iron oxides, bismuth oxychloride, mica

Questions or comments?

1-800-322-2036

Monday - Friday

(10 a.m. - 5 p.m. EST)